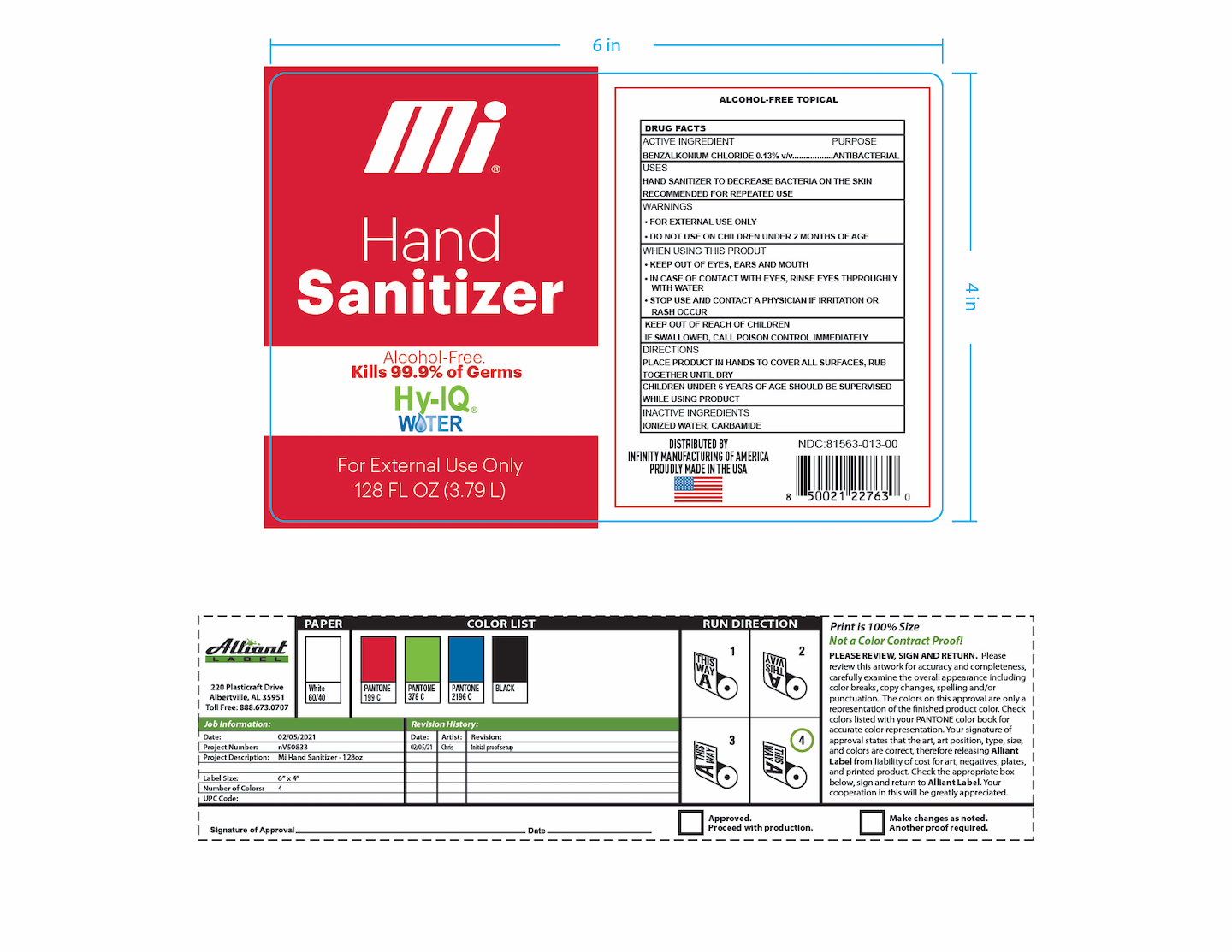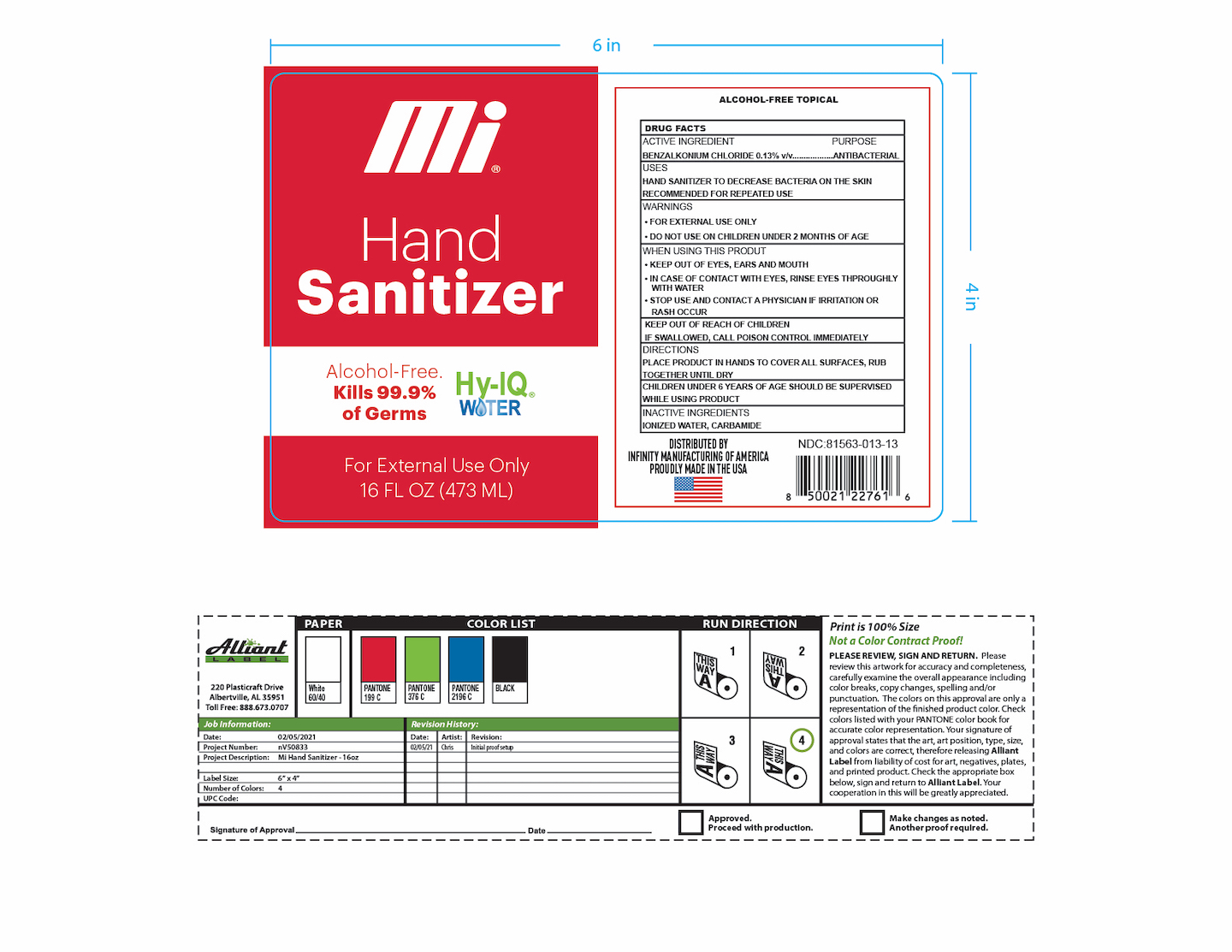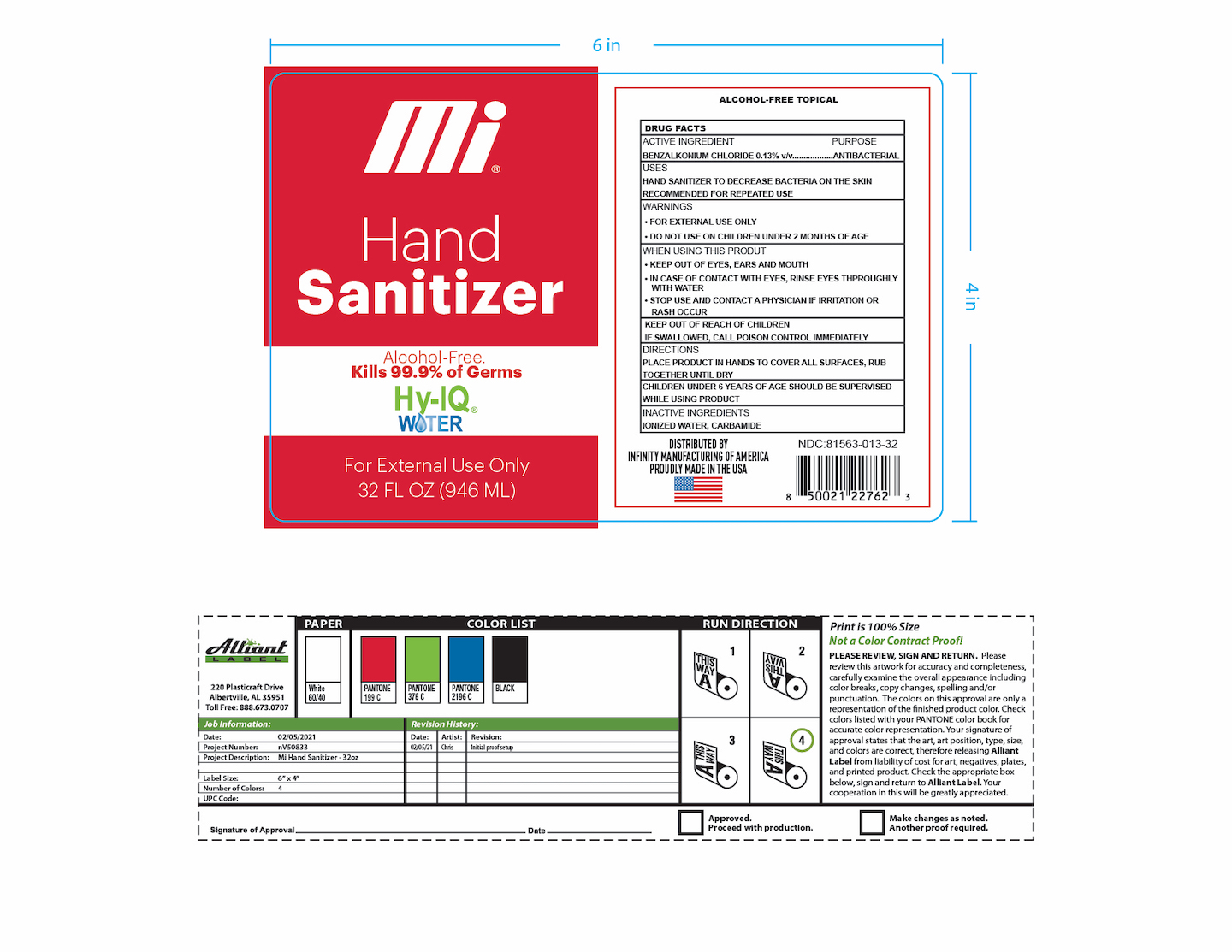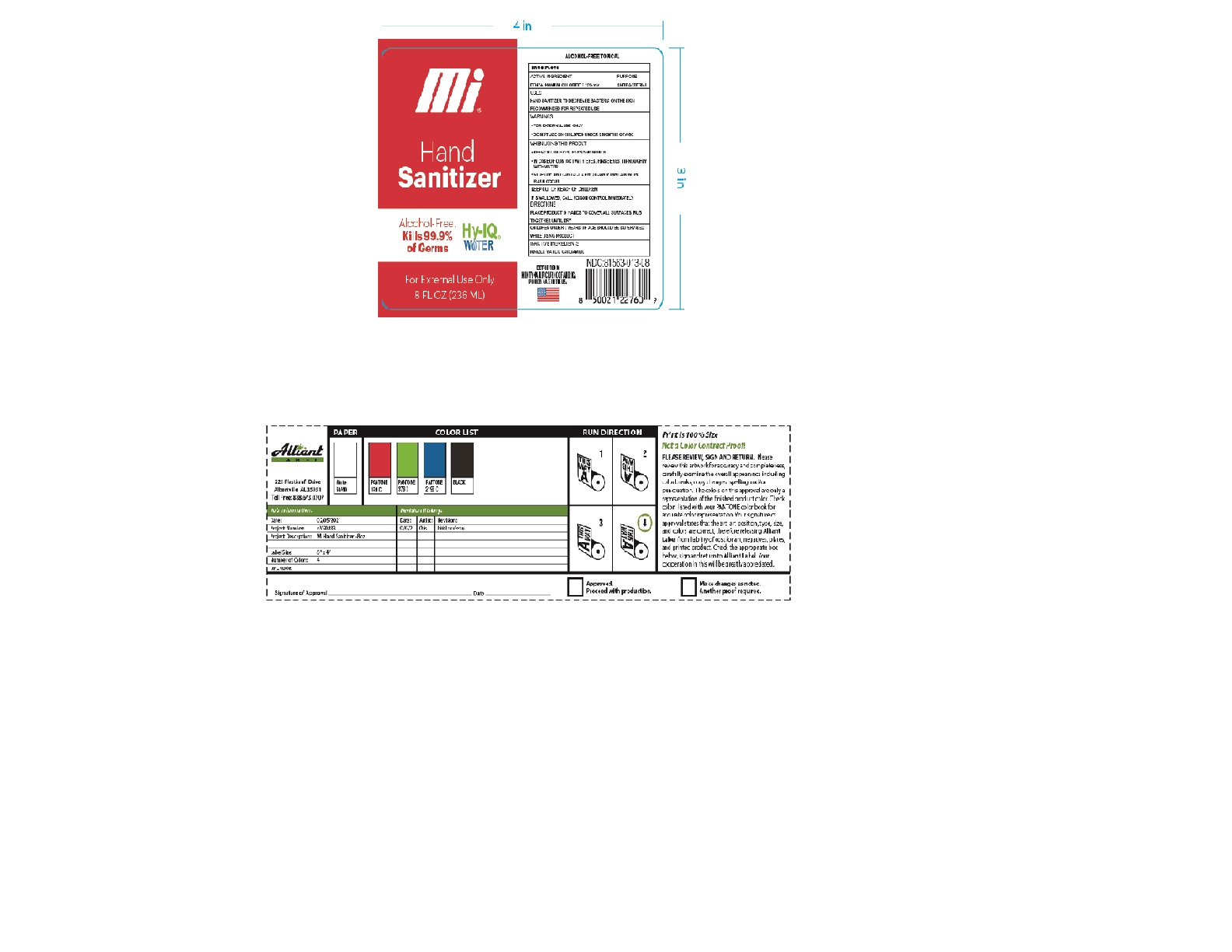 DRUG LABEL: Mi
NDC: 81563-013 | Form: SOLUTION
Manufacturer: Infinity Manufacturing of America, LLC
Category: otc | Type: HUMAN OTC DRUG LABEL
Date: 20210223

ACTIVE INGREDIENTS: BENZALKONIUM CHLORIDE 0.0013 g/1 mL
INACTIVE INGREDIENTS: UREA; WATER

SPL Unclassified Section

This is hand sanitizer manufactured according to OTC Monograph part 333a

Purpose

Antiseptic, Hand Sanitizer

WARNINGS

• FOR EXTERNAL USE ONLY

• DO NOT USE ON CHILDREN UNDER 2 MONTHS OF AGE

WHEN USING THIS PRODUT

• KEEP OUT OF EYES, EARS AND MOUTH

• IN CASE OF CONTACT WITH EYES, RINSE EYES THPROUGHLY WITH WATER

• STOP USE AND CONTACT A PHYSICIAN IF IRRITATION OR

RASH OCCUR

KEEP OUT OF REACH OF CHILDREN

IF SWALLOWED, CALL POISON CONTROL IMMEDIATELY

Do Not Use-OTC

on children less than 2 mos in age on open skin wounds.

When Using Section

When using this product keep out of eyes, ears, and mouth. in case of contact with eyes, rinse eyes thoroughly with water.

Stop use and ask a doctor if irritation or rash occurs. These may be signs of a serious condition.

Keep out of reach of children. If swallowed, get medical help or contact a Poison Control Center right away,

Stop Use Section

Stop use and ask a doctor if irritation or rash occurs. These may be signs of a serious condidtion.

Keep out of reach of children. If swallowed, get medical help or contact a Poison Control Center right away.

DOSAGE AND ADMINISTRATION

PLACE PRODUCT IN HANDS TO COVER ALL SURFACES, RUB

TOGETHER UNTIL DRY

CHILDREN UNDER 6 YEARS OF AGE SHOULD BE SUPERVISED

WHILE USING PRODUCT

INACTIVE INGREDIENTS IONIZED WATER, CARBAMIDE

Storage and Handling

Store between 15-30C (59-86F)

Avoid freezing and excessive heat above 40C(104F)

Inactive Ingredients

Ionized Water, Carbamide

When using this product keep out of eyes, ears, and mouth. in case of contact with eyes, rinse eyes thoroughly with water.

Stop use and ask a doctor if irritation or rash occurs. These may be signs of a serious condition.

Keep out of reach of children. If swallowed, get medical help or contact a Poison Control Center right away,

ACTIVE INGREDIENT

BENZALKONIUM CHLORIDE 0.13% v/v..................ANTIBACTERIAL

Active Ingredients

BENZALKONIUM CHLORIDE 0.13% v/v..................ANTIBACTERIAL

Uses

HAND SANITIZER TO DECREASE BACTERIA ON THE SKIN

RECOMMENDED FOR REPEATED USE

PACKAGE LABEL

473ml NDC:81563-013-16

PACKAGE LABEL

946ml NDC:81563-013-32

PACKAGE LABEL

3785 ml NDC: 81563-013-00

PACKAGE LABEL

236ml NDC: 81563-013-08